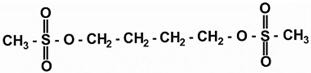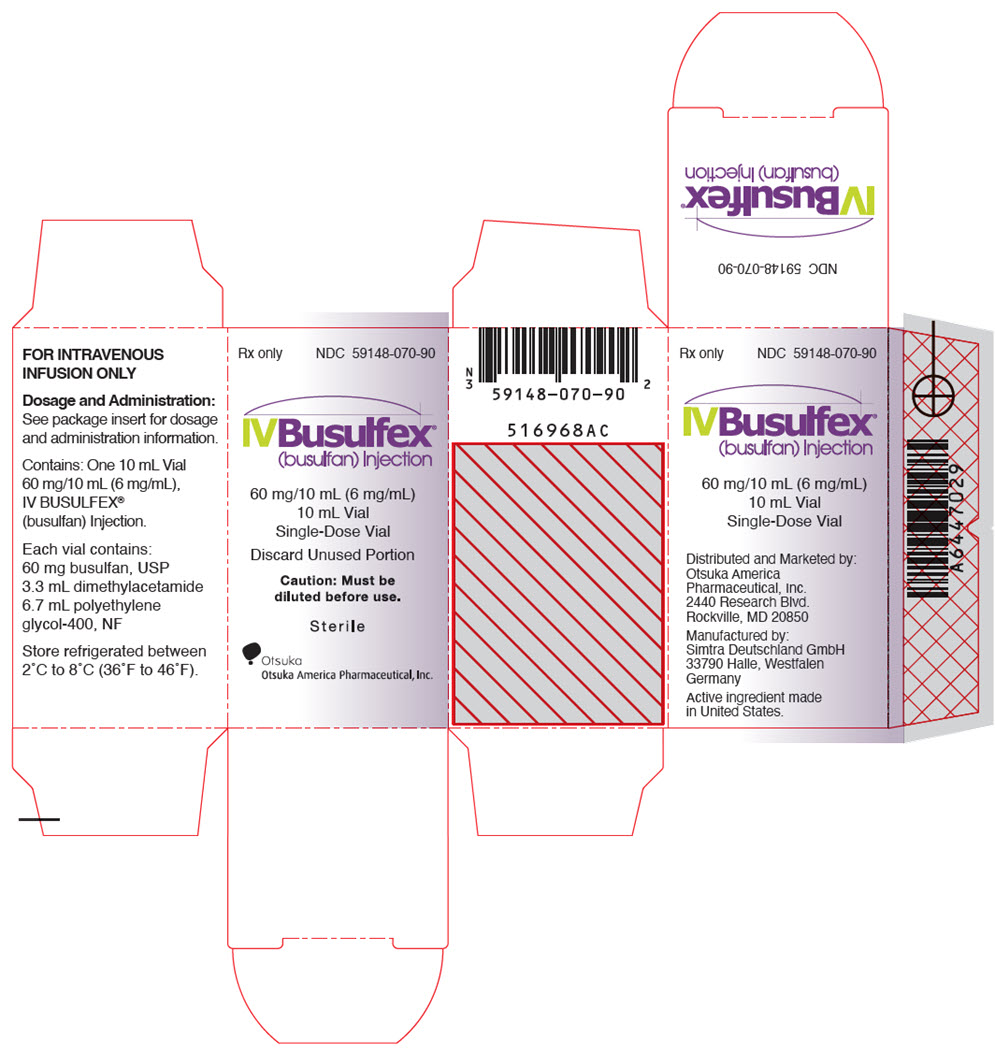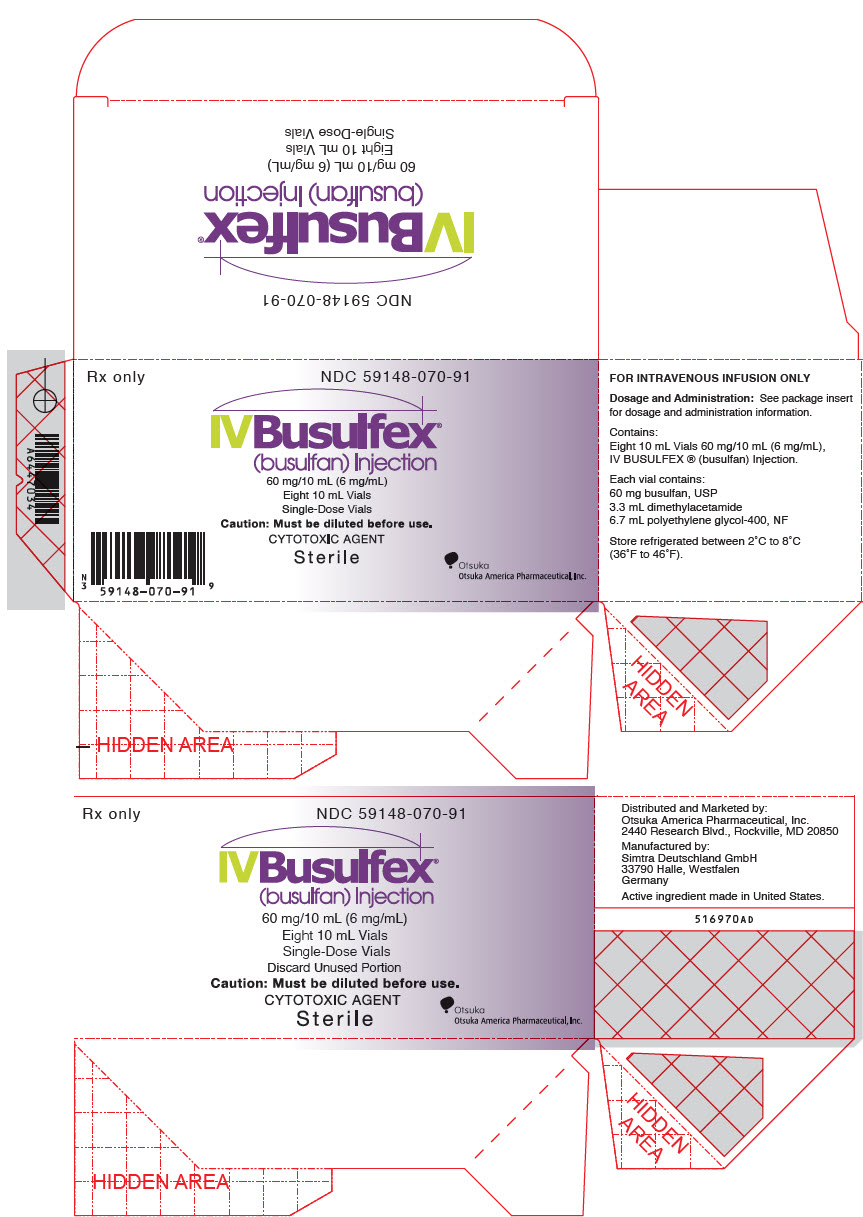 DRUG LABEL: BUSULFEX
NDC: 59148-070 | Form: INJECTION
Manufacturer: Otsuka America Pharmaceutical, Inc.
Category: prescription | Type: HUMAN PRESCRIPTION DRUG LABEL
Date: 20251020

ACTIVE INGREDIENTS: Busulfan 6 mg/1 mL
INACTIVE INGREDIENTS: N,N-dimethylacetamide; Polyethylene Glycol 400

HIGHLIGHTS OF PRESCRIBING INFORMATION

These highlights do not include all the information needed to use BUSULFEX® safely and effectively. See full prescribing information for BUSULFEX.
BUSULFEX (busulfan) Injection, for intravenous use
Initial U.S. Approval: 1999

WARNING: MYELOSUPPRESSION

See full prescribing information for complete boxed warning.

- Causes severe and prolonged myelosuppression. (5.1)
- Hematopoietic progenitor cell transplantation is required to prevent potentially fatal complications of the prolonged myelosuppression. (5.1)

1 INDICATIONS AND USAGE

BUSULFEX is an alkylating drug indicated for:

Use in combination with cyclophosphamide as a conditioning regimen prior to allogeneic hematopoietic progenitor cell transplantation for chronic myelogenous leukemia (CML) (1)

2 DOSAGE AND ADMINISTRATION

- Pre-medicate with anticonvulsants (e.g. benzodiazepines, phenytoin, valproic acid or levetiracetam) and antiemetic (2.1, 5.2)
- Dilute and administer as intravenous infusion. Do not administer as intravenous push or bolus (2.1, 2.3)
- Recommended adult dose: 0.8 mg per kg of ideal body weight or actual body weight, whichever is lower, administered intravenously via a central venous catheter as a two‑hour infusion every six hours for four consecutive days for a total of 16 doses (2.1)

3 DOSAGE FORMS AND STRENGTHS

Injection: 60 mg/10 mL (6 mg/mL) single‑dose vial (3)

4 CONTRAINDICATIONS

BUSULFEX is contraindicated in patients with a history of hypersensitivity to any of its components (4)

5 WARNINGS AND PRECAUTIONS

- Seizures: Initiate anticonvulsant prophylactic therapy prior to treatment with BUSULFEX. Monitor patients with history of seizure disorder, head trauma or receiving epileptogenic drugs (5.2)
- Hepatic Veno-Occlusive Disease (HVOD): Increased risk of developing HVOD at AUC greater than 1,500 micromole per min. Monitor serum transaminases, alkaline phosphatase and bilirubin daily (5.3)
- Embryo-fetal Toxicity: Can cause fetal harm. Advise of potential risk to a fetus and use of effective contraception (5.4, 8.1, 8.3)
- Cardiac tamponade has been reported in pediatric patients with thalassemia who received high doses of oral busulfan and cyclophosphamide. Abdominal pain and vomiting preceded the tamponade in most patients (5.5)

6 ADVERSE REACTIONS

Most common adverse reactions (incidence >60%) were myelosuppression, nausea, stomatitis, vomiting, anorexia, diarrhea, insomnia, fever, hypomagnesemia, abdominal pain, anxiety, headache, hyperglycemia and hypokalemia (6.1)

To report SUSPECTED ADVERSE REACTIONS, contact Otsuka America Pharmaceutical, Inc. at 1-800-438-9927 or FDA at 1-800-FDA-1088 or www.fda.gov/medwatch.

7 DRUG INTERACTIONS

- Drugs that decrease BUSULFEX clearance: Metronidazole, itraconazole, iron chelating agents, acetaminophen. (7.1)
- Drugs that increase BUSULFEX clearance: Phenytoin. (7.2)

8 USE IN SPECIFIC POPULATIONS

Lactation: Advise women not to breastfeed (8.2)

FULL PRESCRIBING INFORMATION

WARNING: MYELOSUPPRESSION

BUSULFEX (busulfan) Injection causes severe and prolonged myelosuppression at the recommended dosage. Hematopoietic progenitor cell transplantation is required to prevent potentially fatal complications of the prolonged myelosuppression [see Warnings and Precautions (5.1)].

1 INDICATIONS AND USAGE

BUSULFEX is indicated for use in combination with cyclophosphamide as a conditioning regimen prior to allogeneic hematopoietic progenitor cell transplantation for chronic myelogenous leukemia.

2 DOSAGE AND ADMINISTRATION

2.1 Initial Dosing Information

- Administer BUSULFEX in combination with cyclophosphamide as a conditioning regimen prior to bone marrow or peripheral blood progenitor cell replacement. For patients weighing more than 12 kg, the recommended doses are:
  - BUSULFEX 0.8 mg per kg (ideal body weight or actual body weight, whichever is lower) intravenously via a central venous catheter as a two‑hour infusion every six hours for four consecutive days for a total of 16 doses (Days -7, -6, -5 and -4).
  - Cyclophosphamide 60 mg per kg intravenously as a one‑hour infusion on each of two days beginning no sooner than six hours following the 16th dose of BUSULFEX (Days -3 and -2).
  - Administer hematopoietic progenitor cells on Day 0.
- Premedicate patients with anticonvulsants (e.g., benzodiazepines, phenytoin, valproic acid or levetiracetam) to prevent seizures reported with the use of high dose BUSULFEX. Administer anticonvulsants 12 hours prior to BUSULFEX to 24 hours after the last dose of BUSULFEX [see Warnings and Precautions (5.2)].
- Administer antiemetics prior to the first dose of BUSULFEX and continue on a fixed schedule through BUSULFEX administration.
- BUSULFEX clearance is best predicted when the BUSULFEX dose is administered based on adjusted ideal body weight. Dosing BUSULFEX based on actual body weight, ideal body weight or other factors can produce significant differences in BUSULFEX clearance among lean, normal and obese patients.
  - Calculate ideal body weight (IBW) as follows (height in cm, and weight in kg):
     | Men: | IBW (kg)=50+0.91× (height in cm -152)
     | Women: | IBW (kg)=45+0.91× (height in cm -152)
  - For obese or severely obese patients, base BUSULFEX dosing on adjusted ideal body weight (AIBW):
    AIBW= IBW +0.25× (actual weight -IBW).

2.2 Preparation and Administration Precautions

BUSULFEX is incompatible with polycarbonate. Do not use any infusion components (syringes, filter needles, intravenous tubing, etc.) containing polycarbonate with BUSULFEX.

Use an administration set with minimal residual hold-up volume (2 mL to 5 mL) for product administration.

BUSULFEX is a cytotoxic drug. Follow applicable special handling and disposal procedures. Skin reactions may occur with accidental exposure. Use gloves when preparing BUSULFEX. If BUSULFEX or diluted BUSULFEX solution contacts the skin or mucosa, wash the skin or mucosa thoroughly with water.

Visually inspect parenteral drug products for particulate matter and discoloration prior to administration whenever the solution and container permit. Do not use if particulate matter is seen in the BUSULFEX vial.

2.3 Preparation for Intravenous Administration

BUSULFEX must be diluted prior to intravenous infusion with either 0.9% Sodium Chloride Injection, USP (normal saline) or 5% Dextrose Injection, USP (D5W). The diluent quantity should be 10 times the volume of BUSULFEX, so that the final concentration of busulfan is approximately 0.5 mg per mL. Calculation of the dose for a 70 kg patient would be performed as follows:

(70 kg patient) × (0.8 mg per kg) ÷ (6 mg per mL) =9.3 mL BUSULFEX (56 mg total dose).

To prepare the final solution for infusion, add 9.3 mL of BUSULFEX to 93 mL of diluent (normal saline or D5W) as calculated below:

(9.3 mL BUSULFEX) × (10) =93 mL of either diluent plus the 9.3 mL of BUSULFEX to yield a final concentration of busulfan of 0.54 mg per mL (9.3 mL × 6 mg per mL ÷102.3 mL = 0.54 mg per mL).

All transfer procedures require strict adherence to aseptic techniques, preferably employing a vertical laminar flow safety hood while wearing gloves and protective clothing.

Always add the BUSULFEX to the diluent, not the diluent to the BUSULFEX. Mix thoroughly by inverting several times. Discard unused portion.

Infusion pumps should be used to administer the diluted BUSULFEX solution. Set the flow rate of the pump to deliver the entire prescribed BUSULFEX dose over two hours. Prior to and following each infusion, flush the indwelling catheter line with approximately 5 mL of 0.9% Sodium Chloride Injection, USP or 5% Dextrose Injection, USP. DO NOT infuse concomitantly with another intravenous solution of unknown compatibility. WARNING: RAPID INFUSION OF BUSULFEX HAS NOT BEEN TESTED AND IS NOT RECOMMENDED.

3 DOSAGE FORMS AND STRENGTHS

Injection: 60 mg/10 mL (6 mg/mL) as a clear, colorless, sterile, solution in a single-dose vial for intravenous use only.

4 CONTRAINDICATIONS

BUSULFEX is contraindicated in patients with a history of hypersensitivity to any of its components.

5 WARNINGS AND PRECAUTIONS

5.1 Myelosuppression

The most frequent serious consequence of treatment with BUSULFEX at the recommended dose and schedule is prolonged myelosuppression, occurring in all patients (100%). Severe granulocytopenia, thrombocytopenia, anemia, or any combination thereof may develop. Hematopoietic progenitor cell transplantation is required to prevent potentially fatal complications of the prolonged myelosuppression. Monitor complete blood counts, including white blood cell differentials, and quantitative platelet counts daily during treatment and until engraftment is demonstrated. Absolute neutrophil counts dropped below 0.5 × 10^9/L at a median of 4 days post-transplant in 100% of patients treated in the BUSULFEX clinical trial. The absolute neutrophil count recovered at a median of 13 days following allogeneic transplantation when prophylactic filgrastim was used in the majority of patients. Thrombocytopenia (less than 25,000/mm^3 or requiring platelet transfusion) occurred at a median of 5 to 6 days in 98% of patients. Anemia (hemoglobin less than 8.0 g/dL) occurred in 69% of patients. Use antibiotic therapy and platelet and red blood cell support when medically indicated.

5.2 Seizures

Seizures have been reported in patients receiving high-dose oral busulfan at doses producing plasma drug levels similar to those achieved following the recommended dosage of BUSULFEX. Despite prophylactic therapy with phenytoin, one seizure (1/42 patients) was reported during an autologous transplantation clinical trial of BUSULFEX. This episode occurred during the cyclophosphamide portion of the conditioning regimen, 36 hours after the last BUSULFEX dose. Initiate phenytoin therapy or any other alternative anti-convulsant prophylactic therapy (e.g., benzodiazepines, valproic acid or levetiracetam) prior to BUSULFEX treatment [see Dosage and Administration (2.1)]. Use caution when administering the recommended dose of BUSULFEX to patients with a history of a seizure disorder or head trauma or who are receiving other potentially epileptogenic drugs.

5.3 Hepatic Veno-Occlusive Disease (HVOD)

Current literature suggests that high busulfan area under the plasma concentration verses time curve (AUC) values (greater than 1,500 micromole per min) may be associated with an increased risk of developing HVOD. Patients who have received prior radiation therapy, greater than or equal to three cycles of chemotherapy, or a prior progenitor cell transplant may be at an increased risk of developing HVOD with the recommended BUSULFEX dose and regimen. Based on clinical examination and laboratory findings, HVOD was diagnosed in 8% (5/61) of patients treated with BUSULFEX in the setting of allogeneic transplantation, was fatal in 2/5 cases (40%), and yielded an overall mortality from HVOD in the entire study population of 2/61 (3%). Three of the five patients diagnosed with HVOD were retrospectively found to meet the Jones' criteria. The incidence of HVOD reported in the literature from the randomized, controlled trials was 7.7% to 12% [see Clinical Studies (14)]. Monitor serum transaminases, alkaline phosphatase, and bilirubin daily through BMT Day +28 to detect hepatotoxicity, which may herald the onset of HVOD.

5.4 Embryo-fetal Toxicity

BUSULFEX can cause fetal harm when administered to a pregnant woman based on animal data. Busulfan was teratogenic in mice, rats, and rabbits. The solvent, DMA, may also cause fetal harm when administered to a pregnant woman based on findings in animals. Advise pregnant women of the potential risk to a fetus. Advise females and males of reproductive potential to use effective contraception during and after treatment with BUSULFEX [see Use in Specific Populations (8.1, 8.3)].

5.5 Cardiac Tamponade

Cardiac tamponade has been reported in pediatric patients with thalassemia (8/400 or 2% in one series) who received high doses of oral busulfan and cyclophosphamide as the preparatory regimen for hematopoietic progenitor cell transplantation. Six of the eight children died and two were saved by rapid pericardiocentesis. Abdominal pain and vomiting preceded the tamponade in most patients. Monitor for signs and symptoms, promptly evaluate and treat if cardiac tamponade is suspected.

5.6 Bronchopulmonary Dysplasia

Bronchopulmonary dysplasia with pulmonary fibrosis is a rare but serious complication following chronic busulfan therapy. The average onset of symptoms is 4 years after therapy (range 4 months to 10 years).

5.7 Cellular Dysplasia

BUSULFEX may cause cellular dysplasia in many organs. Cytologic abnormalities characterized by giant, hyperchromatic nuclei have been reported in lymph nodes, pancreas, thyroid, adrenal glands, liver, lungs and bone marrow. This cytologic dysplasia may be severe enough to cause difficulty in the interpretation of exfoliative cytologic examinations of the lungs, bladder, breast and the uterine cervix.

6 ADVERSE REACTIONS

The following adverse reactions are discussed in more detail in other sections of the labeling:

- Myelosuppression [see Warnings and Precautions (5.1)]
- Seizures [see Warnings and Precautions (5.2)]
- Hepatic Veno-Occlusive Disease (HVOD) [see Warnings and Precautions (5.3)]
- Embryo-fetal Toxicity [see Warnings and Precautions (5.4)]
- Cardiac Tamponade [see Warnings and Precautions (5.5)]
- Bronchopulmonary Dysplasia [see Warnings and Precautions (5.6)]
- Cellular Dysplasia [see Warnings and Precautions (5.7)]

6.1 Clinical Trials Experience

Because clinical trials are conducted under widely varying conditions, adverse reaction rates observed in the clinical trials of a drug cannot be directly compared to rates in the clinical trials of another drug and may not reflect the rates observed in practice.

Adverse reaction information is primarily derived from the clinical study (N=61) of BUSULFEX, and the data obtained for high-dose oral busulfan conditioning in the setting of randomized, controlled trials identified through a literature review.

In the BUSULFEX (busulfan) Injection allogeneic stem cell transplantation clinical trial, all patients were treated with BUSULFEX 0.8 mg per kg as a two‑hour infusion every six hours for 16 doses over four days, combined with cyclophosphamide 60 mg per kg for 2 days. Ninety-three percent (93%) of evaluable patients receiving this dose of BUSULFEX maintained an AUC less than 1,500 micromole per min for dose 9, which has generally been considered the level that minimizes the risk of HVOD.

Table 1 lists the non-hematologic adverse reactions events through Bone Marrow Transplantation (BMT) Day +28 at a rate greater than or equal to 20% in patients treated with BUSULFEX prior to allogeneic hematopoietic cell transplantation.

Table 1: Summary of the Incidence (greater than or equal to 20%) of Non-Hematologic Adverse Reactions through BMT Day +28 in Patients who Received BUSULFEX Prior to Allogeneic Hematopoietic Progenitor Cell Transplantation
Non-Hematological Adverse Reactions [Includes all reported adverse reactions regardless of severity (toxicity grades 1 to4)] | Percent Incidence
BODY AS A WHOLE
Fever | 80
Headache | 69
Asthenia | 51
Chills | 46
Pain | 44
Edema General | 28
Allergic Reaction | 26
Chest Pain | 26
Inflammation at Injection Site | 25
Back Pain | 23
CARDIOVASCULAR SYSTEM
Tachycardia | 44
Hypertension | 36
Thrombosis | 33
Vasodilation | 25
DIGESTIVE SYSTEM
Nausea | 98
Stomatitis (Mucositis) | 97
Vomiting | 95
Anorexia | 85
Diarrhea | 84
Abdominal Pain | 72
Dyspepsia | 44
Constipation | 38
Dry Mouth | 26
Rectal Disorder | 25
Abdominal Enlargement | 23
METABOLIC AND NUTRITIONAL SYSTEM
Hypomagnesemia | 77
Hyperglycemia | 66
Hypokalemia | 64
Hypocalcemia | 49
Hyperbilirubinemia | 49
Edema | 36
SGPT Elevation | 31
Creatinine Increased | 21
NERVOUS SYSTEM
Insomnia | 84
Anxiety | 72
Dizziness | 30
Depression | 23
RESPIRATORY SYSTEM
Rhinitis | 44
Lung Disorder | 34
Cough | 28
Epistaxis | 25
Dyspnea | 25
SKIN AND APPENDAGES
Rash | 57
Pruritus | 28

Additional Adverse Reactions by Body System

Hematologic: Prolonged prothrombin time

Gastrointestinal: Esophagitis, ileus, hematemesis, pancreatitis, rectal discomfort

Hepatic: Alkaline phosphatase increases, jaundice, hepatomegaly

Graft-versus-host disease: Graft-versus-host disease. There were 3 deaths (5%) attributed to GVHD.

Edema: Hypervolemia, or documented weight increase

Infection: Infection, pneumonia (fatal in one patient and life-threatening in 3% of patients)

Cardiovascular: Arrhythmia, atrial fibrillation, ventricular extrasystoles, third degree heart block, thrombosis (all episodes were associated with the central venous catheter), hypotension, flushing and hot flashes, cardiomegaly, ECG abnormality, left-sided heart failure, and pericardial effusion

Pulmonary: Hyperventilation, alveolar hemorrhage (fatal in 3%), pharyngitis, hiccup, asthma, atelectasis, pleural effusion, hypoxia, hemoptysis, sinusitis, and interstitial fibrosis (fatal in a single case)

Neurologic: Cerebral hemorrhage, coma, delirium, agitation, encephalopathy, confusion, hallucinations, lethargy, somnolence

Renal: BUN increased, dysuria, oliguria, hematuria, hemorrhagic cystitis

Skin: Alopecia, vesicular rash, maculopapular rash, vesiculo-bullous rash, exfoliative dermatitis, erythema nodosum, acne, skin discoloration

Metabolic: Hypophosphatemia, hyponatremia

Other Events: Injection site pain, myalgia, arthralgia, ear disorder

6.2 Postmarketing Experience

The following adverse reactions have been identified during post-approval use of BUSULFEX (busulfan) Injection. Because these reactions are reported voluntarily from a population of uncertain size, it is not always possible to reliably estimate their frequency or establish a causal relationship to drug exposure.

Blood and Lymphatic System Disorders: febrile neutropenia

Gastrointestinal Disorders: tooth hypoplasia

Metabolism and Nutrition Disorders: tumor lysis syndrome

Vascular Disorders: thrombotic microangiopathy (TMA)

Infections and Infestations: severe bacterial, viral (e.g., cytomegalovirus viremia) and fungal infections; and sepsis.

6.3 Oral Busulfan Literature Review

A literature review identified four randomized, controlled trials that evaluated a high-dose oral busulfan-containing conditioning regimen for allogeneic bone marrow transplantation in the setting of CML [see Clinical Studies (14)]. The safety outcomes reported in those trials are summarized in Table 2 below for a mixed population of hematological malignancies (AML, CML, and ALL).

Table 2: Summary of safety analyses from the randomized, controlled trials utilizing a high dose oral busulfan-containing conditioning regimen that were identified in a literature review.
Clift
CML Chronic Phase
TRM [TRM = Transplantation Related Mortality] | VOD [VOD = Veno-Occlusive Disease of the liver] | GVHD [GVHD = Graft versus Host Disease] | Pulmonary | Hemorrhagic Cystitis | Seizure
Death ≤100d =4.1% (3/73) | No Report | Acute≥Grade 2=35% Chronic=41% (30/73) | 1 death from Idiopathic Interstitial Pneumonitis And 1 death from Pulmonary Fibrosis | No Report | No Report
Devergie
CML Chronic Phase
TRM | VOD | GVHD | Pulmonary | Hemorrhagic Cystitis | Seizure
38% | 7.7% (5/65) Deaths=4.6% (3/65) | Acute≥Grade 2=41% (24/59 at risk) | Interstitial Pneumonitis=16.9% (11/65) | 10.8% (7/65) | No Report
Ringden
CML, AML, ALL
TRM | VOD | GVHD | Pulmonary | Hemorrhagic Cystitis | Seizure
28% | 12% | Acute≥Grade 2 GVHD=26% Chronic GVHD =45% | Interstitial Pneumonitis =14% | 24% | 6%
Blume
CML, AML, ALL
TRM | VOD | GVHD | Pulmonary | Hemorrhagic Cystitis | Seizure
No Report | Deaths =4.9% | Acute≥Grade 2 GVHD=22% (13/58 at risk) Chronic GVHD =31% (14/45 at risk) | No Report | No Report | No Report

7 DRUG INTERACTIONS

7.1 Drugs that Decrease BUSULFEX Clearance

Itraconazole decreases busulfan clearance by up to 25%. Metronidazole decreases the clearance of busulfan to a greater extent than does itraconazole; metronidazole coadministration has been associated with increased busulfan toxicity. Fluconazole (200 mg) has been used with BUSULFEX.

Decreased clearance of busulfan was observed with concomitant use with deferasirox. The mechanism of this interaction is not fully elucidated. Discontinue iron chelating agents well in advance of administration of BUSULFEX to avoid increased exposure to busulfan.

Because busulfan is eliminated from the body via conjugation with glutathione, use of acetaminophen prior to (less than 72 hours) or concurrent with BUSULFEX may result in reduced busulfan clearance based upon the known property of acetaminophen to decrease glutathione levels in the blood and tissues.

7.2 Drugs that Increase BUSULFEX Clearance

Phenytoin increases the clearance of busulfan by 15% or more, possibly due to the induction of glutathione-S-transferase. Since the pharmacokinetics of BUSULFEX were studied in patients treated with phenytoin, the clearance of BUSULFEX at the recommended dose may be lower and exposure (AUC) higher in patients not treated with phenytoin.

8 USE IN SPECIFIC POPULATIONS

8.1 Pregnancy

Risk Summary

BUSULFEX can cause fetal harm when administered to a pregnant woman based on animal data. Busulfan was teratogenic in mice, rats, and rabbits following administration during organogenesis. The solvent, DMA, may also cause fetal harm when administered to a pregnant woman. In rats, DMA doses of approximately 40% of the daily dose of DMA in the BUSULFEX dose on a mg/m^2 basis given during organogenesis caused significant developmental anomalies (see Data). There are no available human data informing the drug-associated risk. Advise pregnant women of the potential risk to a fetus.

The background risk of major birth defects and miscarriage for the indicated populations are unknown. However, the background risk in the U.S. general population of major birth defects is 2 to 4% and of miscarriage is 15 to 20% of clinically recognized pregnancies.

Data

Animal Data

Following administration during organogenesis in animals, busulfan caused malformations and anomalies, including significant alterations in the musculoskeletal system, body weight gain, and size. In pregnant rats, busulfan produced sterility in both male and female offspring due to the absence of germinal cells in the testes and ovaries. The solvent, N,N-dimethylacetamide (DMA), administered to rats at doses of 400 mg/kg/day (about 40% of the daily dose of DMA in the BUSULFEX dose on a mg/m^2 basis) during organogenesis caused significant developmental anomalies. The most striking abnormalities included anasarca, cleft palate, vertebral anomalies, rib anomalies, and serious anomalies of the vessels of the heart.

8.2 Lactation

Risk Summary

It is not known whether BUSULFEX is present in human milk. Because many drugs are excreted in human milk and because of the potential for tumorigenicity shown for busulfan in human and animal studies, discontinue breastfeeding during treatment with BUSULFEX.

8.3 Females and Males of Reproductive Potential

Contraception

Females

BUSULFEX can cause fetal harm when administered to a pregnant woman [see Use in Specific Populations (8.1)]. Advise females of reproductive potential to use effective contraception during treatment with BUSULFEX and for 6 months following cessation of therapy.

Males

BUSULFEX may damage spermatozoa and testicular tissue, resulting in possible genetic fetal abnormalities. Males with female sexual partners of reproductive potential should use effective contraception during treatment with BUSULFEX and for 3 months after cessation of therapy [see Nonclinical Toxicology (13.1)].

Infertility

Females

Ovarian suppression and amenorrhea commonly occur in premenopausal women undergoing chronic, low-dose busulfan therapy for chronic myelogenous leukemia. BUSULFEX may cause temporary or permanent infertility in prepubertal girls or in females of child-bearing potential treated with high-dose BUSULFEX in the conditioning regimen prior to allogeneic hematopoietic progenitor cell transplantation.

Males

Sterility, azoospermia, and testicular atrophy have been reported in male patients.

8.4 Pediatric Use

The effectiveness of BUSULFEX in the treatment of CML has not been specifically studied in pediatric patients. An open-label, uncontrolled study evaluated the pharmacokinetics of BUSULFEX in 24 pediatric patients receiving BUSULFEX as part of a conditioning regimen administered prior to hematopoietic progenitor cell transplantation for a variety of malignant hematologic (N=15) or non-malignant diseases (N=9). Patients ranged in age from 5 months to 16 years (median 3 years). BUSULFEX dosing was targeted to achieve an area under the plasma concentration curve (AUC) of 900-1350 micromole per min with an initial dose of 0.8 mg per kg or 1.0 mg per kg (based on Actual Body Weight (ABW)) if the patient was greater than 4 or less than or equal to 4 years, respectively. The dose was adjusted based on plasma concentration after completion of dose 1.

Patients received BUSULFEX doses every six hours as a two‑hour infusion over four days for a total of 16 doses, followed by cyclophosphamide 50 mg per kg once daily for four days. After one rest day, hematopoietic progenitor cells were infused. All patients received phenytoin as seizure prophylaxis. The target AUC (900-1350±5% micromole per min) for BUSULFEX was achieved at Dose 1 in 71% (17/24) of patients. Steady state pharmacokinetic testing was performed at Dose 9 and 13. BUSULFEX levels were within the target range for 21 of 23 evaluable patients.

All 24 patients experienced neutropenia (absolute neutrophil count (ANC) less than 0.5 × 10^9/L) and thrombocytopenia (platelet transfusions or platelet count less than 20,000/mm^3). Seventy-nine percent (19/24) of patients experienced lymphopenia (absolute lymphocyte count less than 0.1×10^9). In 23 patients, the ANC recovered to greater than 0.5 × 10^9/L (median time to recovery = BMT Day +13; range = BMT Day +9 to +22). One patient who died on Day +20 had not recovered to an ANC >0.5 × 10^9/L.

Four (17%) patients died during the study. Two patients died within 28 days of transplant: one with pneumonia and capillary leak syndrome, and the other with pneumonia and veno-occlusive disease. Two patients died prior to Day 100; one due to progressive disease and one due to multi-organ failure.

Adverse reactions were reported in all 24 patients during the study period (BMT Day -10 through BMT Day +28) or post-study surveillance period (Day +29 through +100). These included vomiting (100%), nausea (83%), stomatitis (79%), HVOD (21%), graft-versus host disease (GVHD) (25%), and pneumonia (21%).

Based on the results of this 24‑patient clinical trial, a suggested dosing regimen of BUSULFEX in pediatric patients is shown in the following dosing nomogram:

BUSULFEX Dosing Nomogram
Patient's Actual Body Weight (ABW) | BUSULFEX Dosage
less than or equal to12 kgs | 1.1 (mg per kg)
greater than 12 kgs | 0.8 (mg per kg)

Simulations based on a pediatric population pharmacokinetic model indicate that approximately 60% of pediatric patients will achieve a target BUSULFEX exposure (AUC) between 900 to 1350 micromole per min with the first dose of BUSULFEX using this dosing nomogram. Therapeutic drug monitoring and dose adjustment following the first dose of BUSULFEX is recommended.

Dose Adjustment Based on Therapeutic Drug Monitoring

Instructions for measuring the AUC of busulfan at Dose 1 (see Blood Sample Collection for AUC Determination) and the formula for adjustment of subsequent doses to achieve the desired target AUC (1125 micromole per min), are provided below.

Adjusted dose (mg) = Actual dose (mg) × Target AUC (micromole per min)/Actual AUC (micromole per min)

For example, if a patient received a dose of 11 mg busulfan and if the corresponding AUC measured was 800 micromole per min, for a target AUC of 1125 micromole per min, the target mg dose would be:

Mg dose =11 mg × 1125 micromole per min /800 micromole per min =15.5 mg

BUSULFEX dose adjustment may be made using this formula and instructions below.

Blood Sample Collection for AUC Determination

Calculate the AUC (micromole per min) based on blood samples collected at the following time points:

For dose 1:2 hour (end of infusion), 4 hour and 6 hour (immediately prior to the next scheduled BUSULFEX administration). Actual sampling times should be recorded.

For doses other than Dose 1: Pre-infusion (baseline), 2 hour (end of infusion), 4 hour and 6 hour (immediately prior to the next scheduled BUSULFEX administration).

AUC calculations based on fewer than the three specified samples may result in inaccurate AUC determinations.

For each scheduled blood sample, collect one to three mL of blood into heparinized (Na or Li heparin) Vacutainer® tubes. The blood samples should be placed on wet ice immediately after collection and should be centrifuged (at 4°C) within one hour. The plasma, harvested into appropriate cryovial storage tubes, is to be frozen immediately at -20°C. All plasma samples are to be sent in a frozen state (i.e., on dry ice) to the assay laboratory for the determination of plasma busulfan concentrations.

Calculation of AUC

BUSULFEX AUC calculations may be made using the following instructions and appropriate standard pharmacokinetic formula:

Dose 1 AUCinfinity Calculation: AUCinfinity = AUC0-6hr +AUCextrapolated, where AUC0-6hr is to be estimated using the linear trapezoidal rule and AUC extrapolated can be computed by taking the ratio of the busulfan concentration at Hour 6 and the terminal elimination rate constant, λz. The λz must be calculated from the terminal elimination phase of the busulfan concentration vs. time curve. A "0" pre-dose busulfan concentration should be assumed; and used in the calculation of AUC.

If the AUC is assessed subsequent to Dose 1, steady-state AUCss (AUC0-6hr) is to be estimated from the trough, 2 hour, 4 hour and 6 hour concentrations using the linear trapezoidal rule.

Instructions for Drug Administration and Blood Sample Collection for Therapeutic Drug Monitoring

Use an administration set with minimal residual hold up (priming) volume (1 to 3 mL) for drug infusion to ensure accurate delivery of the entire prescribed dose and to ensure accurate collection of blood samples for therapeutic drug monitoring and dose adjustment.

Prime the administration set tubing with drug solution to allow accurate documentation of the start time of BUSULFEX infusion. Collect the blood sample from a peripheral IV line to avoid contamination with infusing drug. If the blood sample is taken directly from the existing central venous catheter (CVC), DO NOT COLLECT THE BLOOD SAMPLE WHILE THE DRUG IS INFUSING to ensure that the end of infusion sample is not contaminated with any residual drug. At the end of infusion (2 hour), disconnect the administration tubing and flush the CVC line with 5 mL of normal saline prior to the collection of the end of infusion sample from the CVC port. Collect the blood samples from a different port than that used for the BUSULFEX infusion. When recording the BUSULFEX infusion stop time, do not include the time required to flush the indwelling catheter line. Discard the administration tubing at the end of the two‑hour infusion [see Dosage and Administration (2.3)].

8.5 Geriatric Use

Clinical studies of BUSULFEX did not include sufficient numbers of subjects aged 65 and over to determine whether they respond differently from younger subjects.

10 OVERDOSAGE

There is no known antidote to BUSULFEX other than hematopoietic progenitor cell transplantation. In the absence of hematopoietic progenitor cell transplantation, the recommended dosage for BUSULFEX would constitute an overdose of busulfan. The principal toxic effect is profound bone marrow hypoplasia/aplasia and pancytopenia, but the central nervous system, liver, lungs, and gastrointestinal tract may be affected. Monitor hematologic status closely and institute vigorous supportive measures as medically indicated. Survival after a single 140 mg dose of Myleran® tablets in an 18 kg, 4-year-old child has been reported. Inadvertent administration of a greater than normal dose of oral busulfan (2.1 mg per kg; total dose of 23.3 mg per kg) occurred in a 2-year-old child prior to a scheduled bone marrow transplant without sequelae. An acute dose of 2.4 g was fatal in a 10-year-old boy. There is one report that busulfan is dialyzable, thus dialysis should be considered in the case of overdose.

11 DESCRIPTION

Busulfan is a bifunctional alkylating agent known chemically as 1,4-butanediol, dimethanesulfonate. The molecular formula of busulfan is CH3SO2O(CH2)4OSO2CH3 with a molecular weight of 246 g/mole. Busulfan has the following chemical structure:

BUSULFEX (busulfan) Injection is supplied as a clear, colorless, sterile, solution in 10 mL single-dose vials for intravenous administration upon dilution. Each vial contains 60 mg of busulfan in N,N-dimethylacetamide (DMA), 3.3 mL and Polyethylene Glycol 400, NF 6.7 mL. The solubility of busulfan in water is 0.1 g per L and the pH of BUSULFEX diluted to approximately 0.5 mg per mL busulfan in 0.9% Sodium Chloride Injection, USP or 5% Dextrose Injection, USP as recommended for infusion reflects the pH of the diluent used and ranges from 3.4 to 3.9.

12 CLINICAL PHARMACOLOGY

12.1 Mechanism of Action

Busulfan is a bifunctional alkylating agent in which two labile methanesulfonate groups are attached to opposite ends of a four-carbon alkyl chain. In aqueous media, busulfan hydrolyzes to release the methanesulfonate groups. This produces reactive carbonium ions that can alkylate DNA. DNA damage is thought to be responsible for much of the cytotoxicity of busulfan.

12.3 Pharmacokinetics

The pharmacokinetics of BUSULFEX were studied in 59 patients participating in a prospective trial of a BUSULFEX-cyclophosphamide preparatory regimen prior to allogeneic hematopoietic progenitor stem cell transplantation. Patients received 0.8 mg/kg BUSULFEX every six hours, for a total of 16 doses over four days. Fifty-five of fifty-nine patients (93%) administered BUSULFEX maintained AUC values below the target value (less than1500 micromole per min).

Table 3: Steady State Pharmacokinetic Parameters Following BUSULFEX® (busulfan) Infusion (0.8 mg per kg; N=59)
 | Mean | CV (%) | Range
Cmax (ng per mL) | 1222 | 18 | 496-1684
AUC (micromole per min) | 1167 | 20 | 556-1673
CL (mL per min per kg) [Clearance normalized to actual body weight for all patients.] | 2.52 | 25 | 1.49-4.31

BUSULFEX pharmacokinetics showed consistency between Dose 9 and Dose 13 as demonstrated by reproducibility of steady state Cmax and a low coefficient of variation for this parameter.

Distribution: Busulfan achieves concentrations in the cerebrospinal fluid approximately equal to those in plasma. Busulfan primarily binds to albumin (Mean ± standard deviation=32.4 ± 2.2%).

Metabolism: Busulfan is predominantly metabolized by conjugation with glutathione, both spontaneously and by glutathione S-transferase (GST) catalysis. This conjugate undergoes extensive oxidative metabolism in the liver.

Excretion: Following administration of ^14C-labeled busulfan to humans, approximately 30% of the radioactivity was excreted into the urine over 48 hours; negligible amounts were recovered in feces.

Specific Populations

Pediatric Patients: In a pharmacokinetic study of BUSULFEX in 24 pediatric patients, the population pharmacokinetic (PPK) estimates of BUSULFEX for clearance (CL) and volume of distribution (V) were determined. For actual body weight, PPK estimates of CL and V were 4.04 L/hr per 20 kg (3.37 mL per min per kg; interpatient variability 23%); and 12.8 L per 20 kg (0.64 L per kg; interpatient variability 11%).

13 NONCLINICAL TOXICOLOGY

13.1 Carcinogenesis, Mutagenesis, Impairment of Fertility

Busulfan is a mutagen and a clastogen. In in vitro tests it caused mutations in Salmonella typhimurium and Drosophila melanogaster. Chromosomal aberrations induced by busulfan have been reported in vivo (rats, mice, hamsters, and humans) and in vitro (rodent and human cells). The intravenous administration of busulfan (48 mg/kg given as biweekly doses of 12 mg/kg, or 30% of the total BUSULFEX dose on a mg/m^2 basis) has been shown to increase the incidence of thymic and ovarian tumors in mice.

Busulfan depleted oocytes of female rats and induced sterility in male rats and hamsters. The solvent DMA may also impair fertility. A DMA daily dose of 0.45 g/kg/day given to rats for nine days (equivalent to 44% of the daily dose of DMA contained in the recommended dose of BUSULFEX on a mg/m^2 basis) significantly decreased spermatogenesis in rats. A single subcutaneous dose of 2.2 g/kg (27% of the total DMA dose contained in BUSULFEX on a mg/m^2 basis) four days after insemination terminated pregnancy in 100% of tested hamsters [see Use in Specific Populations (8.3)].

14 CLINICAL STUDIES

Documentation of the safety and efficacy of busulfan as a component of a conditioning regimen prior to allogeneic hematopoietic progenitor cell reconstitution is derived from two sources:

i) analysis of a prospective clinical trial of BUSULFEX that involved 61 patients diagnosed with various hematologic malignancies, and

ii) the published reports of randomized, controlled trials that employed high-dose oral busulfan as a component of a conditioning regimen for transplantation, which were identified in a literature review of five established commercial databases.

Prospective Clinical Trial of BUSULFEX

The prospective trial was a single-arm, open-label study in 61 patients who received BUSULFEX as part of a conditioning regimen for allogeneic hematopoietic stem cell transplantation. The study included patients with acute leukemia past first remission (first or subsequent relapse), with high-risk first remission, or with induction failure; chronic myelogenous leukemia (CML) in chronic phase, accelerated phase, or blast crisis; primary refractory or resistant relapsed Hodgkin's disease or non-Hodgkin's lymphoma; and myelodysplastic syndrome. Forty-eight percent of patients (29/61) were heavily pretreated, defined as having at least one of the following: prior radiation, greater than or equal to 3 prior chemotherapeutic regimens, or prior hematopoietic stem cell transplant. Seventy-five percent of patients (46/61) were transplanted with active disease.

Patients received 16 BUSULFEX doses of 0.8 mg per kg every 6 hours as a two‑hour infusion for 4 days, followed by cyclophosphamide 60 mg per kg once per day for two days (BuCy2 regimen). All patients received 100% of their scheduled BUSULFEX regimen. No dose adjustments were made. After one rest day, allogeneic hematopoietic progenitor cells were infused. The efficacy parameters in this study were myeloablation (defined as one or more of the following: absolute neutrophil count [ANC] less than 0.5×10^9/L, absolute lymphocyte count [ALC] less than 0.1×10^9/L, thrombocytopenia defined as a platelet count less than 20,000/mm^3 or a platelet transfusion requirement) and engraftment (ANC greater than or equal to 0.5×10^9/L).

All patients (61/61) experienced myeloablation. The median time to neutropenia was 4 days. All evaluable patients (60/60) engrafted at a median of 13 days post-transplant (range 9 to 29 days); one patient was considered non-evaluable because he died of a fungal pneumonia 20 days after BMT and before engraftment occurred. All but 13 of the patients were treated with prophylactic G-CSF. Evidence of donor cell engraftment and chimerism was documented in all patients who had a chromosomal sex marker or leukemic marker (43/43), and no patient with chimeric evidence of allogeneic engraftment suffered a later loss of the allogeneic graft. There were no reports of graft failure in the overall study population. The median number of platelet transfusions per patient was 6, and the median number of red blood cell transfusions per patient was 4.

Twenty-three patients (38%) relapsed at a median of 183 days post-transplant (range 36 to 406 days). Sixty-two percent of patients (38/61) were free from disease with a median follow-up of 269 days post-transplant (range 20 to 583 days). Forty-three patients (70%) were alive with a median follow up of 288 days post-transplant (range 51 to 583 days). There were two deaths before BMT Day +28 and six additional patients died by BMT Day +100. Ten patients (16%) died after BMT Day +100, at a median of 199 days post-transplant (range 113 to 275 days).

Oral Busulfan Literature Review:

Four publications of randomized, controlled trials that evaluated a high-dose oral busulfan-containing conditioning regimen (busulfan 4 mg/kg/d ×4 days + cyclophosphamide 60 mg/kg/d ×2 days) for allogeneic transplantation in the setting of CML were identified. Two of the studies (Clift and Devergie) had populations confined to CML in chronic phase that were randomized between conditioning with busulfan/cyclophosphamide (BU/CY) and cyclophosphamide/total body irradiation (CY/TBI). A total of 138 patients were treated with BU/CY in these studies. The populations of the two remaining studies (Ringden and Blume) included patients with CML, acute lymphoblastic leukemia (ALL), and acute myelogenous leukemia (AML). In the Nordic BMT Group study published by Ringden, et al., 57 patients had CML, and of those, 30 were treated with BU/CY. Patients with CML in chronic phase, accelerated phase, and blast crisis were eligible for this study. The participants with CML (34/122 patients) in a SWOG study published by Blume, et al., had disease beyond first chronic phase. Twenty of those CML patients were treated with BU/CY, and the TBI comparator arm utilized etoposide instead of cyclophosphamide.

Table 4 summarizes the efficacy analyses reported from these 4 studies.

Table 4: Summary of efficacy analyses from the randomized, controlled trials utilizing a high dose oral busulfan-containing conditioning regimen identified in a literature review.
Clift, 1994
CML Chronic Phase
3-year Overall Survival |  | 3-year DFS (p=0.43) |  | Relapse |  | Time to Engraftment (ANC greater than or equal to 500)
BU/CY | CY/TBI | BU/CY | CY/TBI | BU/CY | CY/TBI | BU/CY | CY/TBI
80% | 80% | 71% | 68% | 13% | 13% | 22.6 days | 22.3 days
Devergie, 1995
CML Chronic Phase
5-year Overall Survival |  | 5-year DFS (p=0.75) |  | Relapse (Relative Risk analysis BU/CY:CY/TBI) |  | Time to Engraftment (ANC greater than or equal to 500)
(p=0.5) |  |  |  | (p=0.04)
BU/CY | CY/TBI | BU/CY | CY/TBI | BU/CY | CY/TBI | BU/CY | CY/TBI
60.6% ±11.7% | 65.8% ±12.5% | 59.1% ±11.8% | 51.0% ±14% | 4.10 (95%CI =1.00-20.28) |  | None Given | None Given
Ringden, 1994
CML, AML, ALL
3-year Overall Survival (p<0.03) |  | 3-year Relapse Free Survival (p=0.065) |  | Relapse (p=0.9) |  | Time to Engraftment (ANC greater than 500)
BU/CY | CY/TBI | BU/CY | CY/TBI | BU/CY | CY/TBI | BU/CY | CY/TBI
62% | 76% | 56% | 67% | 22% | 26% | 20 days | 20 days
Blume, 1993 [Eto = etoposide. TBI was combined with etoposide in the comparator arm of this study.]
CML, AML, ALL; Relative Risk Analysis BU/CY: Etoposide/TBI
RR of Mortality |  | DFS |  | RR of Relapse (Relative Risk analysis BU/CY:Eto/TBI) |  | Time to Engraftment
BU/CY | Eto/TBI | BU/CY | Eto/TBI | BU/CY | Eto/TBI | BU/CY | Eto/TBI
0.97 (95% CI=0.64-1.48) |  | Not Given |  | 1.02 (95% CI=0.56-1.86) |  | Not Given
BU = Busulfan
CY = Cyclophosphamide
TBI = Total Body Irradiation
DFS = Disease Free Survival
ANC = Absolute Neutrophil Count

15 REFERENCES

1. OSHA Hazardous Drugs. OSHA. [Accessed on June 18, 2014, from http://www.osha.gov/SLTC/hazardousdrugs/index.html]

16 HOW SUPPLIED/STORAGE AND HANDLING

BUSULFEX is packaged as a sterile solution in 10 mL single-dose clear glass vials - NDC 59148-070-90.

BUSULFEX is distributed as a unit carton of eight vials - NDC 59148-070-91.

STORAGE AND HANDLING

Unopened vials of BUSULFEX must be stored under refrigerated conditions between 2°C to 8°C (36°F to 46°F). Discard unused portion.

BUSULFEX diluted in 0.9% Sodium Chloride Injection, USP, or 5% Dextrose Injection, USP, is stable at room temperature (25°C) for up to 8 hours, but the infusion must be completed within that time.

BUSULFEX diluted in 0.9% Sodium Chloride Injection, USP, is stable at refrigerated conditions (2°C to 8°C) for up to 12 hours but the infusion must be completed within that time.

BUSULFEX is a cytotoxic drug. Follow applicable special handling and disposal procedures^1.

17 PATIENT COUNSELING INFORMATION

Myelosuppression

Advise patients of the possibility of developing low blood cell counts and the need for hematopoietic progenitor cell infusion. Instruct patients to immediately report to their healthcare provider if fever develops [see Warnings and Precautions (5.1)].

Seizures

Advise patients of the possibility of seizures and that they will be given medication to prevent them. Patients should be asked to report a history of seizure or head trauma [see Warnings and Precautions (5.2)].

Hepatic Veno-Occlusive Disease (HVOD)

Advise patients of the risks associated with the use of BUSULFEX as well as the plan for regular blood monitoring during therapy. Specifically inform patients of the following: The risk of veno-occlusive liver disease [see Warnings and Precautions (5.3)].

Embryo-fetal Toxicity

Advise females of reproductive potential of the potential risk to a fetus and to inform their healthcare provider with a known or suspected pregnancy [see Warnings and Precautions (5.4) and Use in Specific Populations (8.1)].

Females of Reproductive Potential

Advise females of reproductive potential to use effective contraception during treatment with BUSULFEX and for 6 months following cessation of therapy [see Use in Specific Populations (8.3)].

Males of Reproductive Potential

Advise males with female sexual partners of reproductive potential to use effective contraception during treatment with BUSULFEX and for 3 months following cessation of therapy [see Use in Specific Populations (8.3)].

Lactation

Advise females to discontinue breastfeeding during treatment with BUSULFEX [see Use in Specific Populations (8.2)].

Infertility

Advise females and males of reproductive potential that BUSULFEX may cause temporary or permanent infertility [see Use in Specific Populations (8.3)].

Cardiac Tamponade

Advise patients of the risk of cardiac tamponade. Instruct patients to report to their healthcare provider symptoms of abdominal pain and vomiting [see Warnings and Precautions (5.5)].

Bronchopulmonary Dysplasia

Advise patients of the possibility of bronchopulmonary dysplasia with pulmonary fibrosis with chronic BUSULFEX therapy. Instruct patients to report symptoms of shortness of breath and cough to their healthcare provider. These symptoms could occur several months or years after therapy with BUSULFEX [see Warnings and Precautions (5.6)].

Distributed and Marketed by:
Otsuka America Pharmaceutical, Inc.
Rockville, MD 20850

Manufactured by:
Simtra Deutschland GmbH
33790 Halle, Westfalen
Germany

©2025 Otsuka Pharmaceutical Co., Ltd., Tokyo, 101-8535 Japan

PRINCIPAL DISPLAY PANEL - 10 mL Vial Carton

Rx only

NDC 59148-070-90

IVBusulfex®
(busulfan) Injection

60 mg/10 mL (6 mg/mL)
10 mL Vial
Single-Dose Vial

Discard Unused Portion

Caution: Must be
diluted before use.

Sterile

Otsuka
Otsuka America Pharmaceutical, Inc.

PRINCIPAL DISPLAY PANEL - Eight 10 mL Vials Carton

Rx only

NDC 59148-070-91

IVBusulfex®
(busulfan) Injection

60 mg/10 mL (6 mg/mL)
Eight 10 mL Vials
Single-Dose Vials
Discard Unused Portion

Caution: Must be diluted before use.

CYTOTOXIC AGENT

Sterile

Otsuka
Otsuka America Pharmaceutical, Inc.